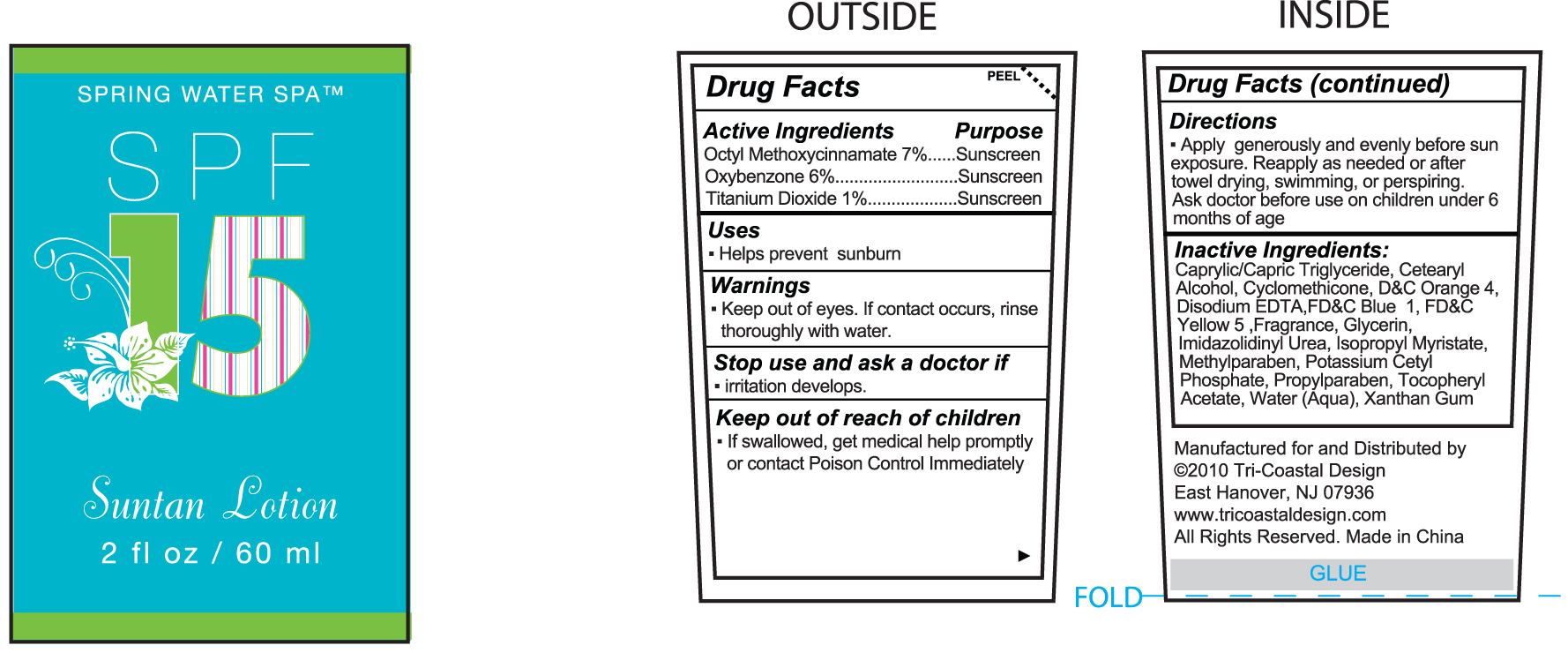 DRUG LABEL: Suntan Lotion
NDC: 49852-201 | Form: LOTION
Manufacturer: Tri-Coastal Design Company Inc. 
Category: otc | Type: HUMAN OTC DRUG LABEL
Date: 20100210

ACTIVE INGREDIENTS: OCTINOXATE 7 mL/100 mL; OXYBENZONE 6 mL/100 mL; TITANIUM DIOXIDE 1 mL/100 mL
INACTIVE INGREDIENTS: MEDIUM-CHAIN TRIGLYCERIDES; CETOSTEARYL ALCOHOL; CYCLOMETHICONE; D&C ORANGE NO. 4; EDETATE DISODIUM; FD&C BLUE NO. 1; FD&C YELLOW NO. 5; GLYCERIN; ISOPROPYL MYRISTATE; METHYLPARABEN; POTASSIUM CETYL PHOSPHATE; PROPYLPARABEN; WATER; XANTHAN GUM

Drug Facts

Active Ingredient

Octyl Methoxycinnamate 7%

Oxybenzone 6%

Titanium Dioxide 1%

Purpose

Sunscreen

Uses

- Helps prevent sunburn

Warnings

- Keep out of eyes. If contact occurs, rinse thoroughly with water.

Stop use and ask a doctor if

- irritation develops

Keep out of reach of children

- If swallowed, get medical help promptly or contact Poison Control immediately.

Directions

- Apply generously and evenly before sun exposure. Reapply as needed or after towel drying, swimming or perspiring. Ask doctor before use on children under 6 months of age

Inactive Ingredients

Caprylic/Capric Triglyceride, Cetearyl Alcohol, Cylcomethicone, DC Orange 4, Disodium EDTA, FDC Blue 1, FDC Yellow 5, Fragrance, Glycerin, Imidazolidinyl Urea, Isopropyl Myristate, Methylparaben, Potassium Cetyl Phosphate, Propylparaben, Tocopheryl Acetate, Water (Aqua), Xanthan Gum

Package Label